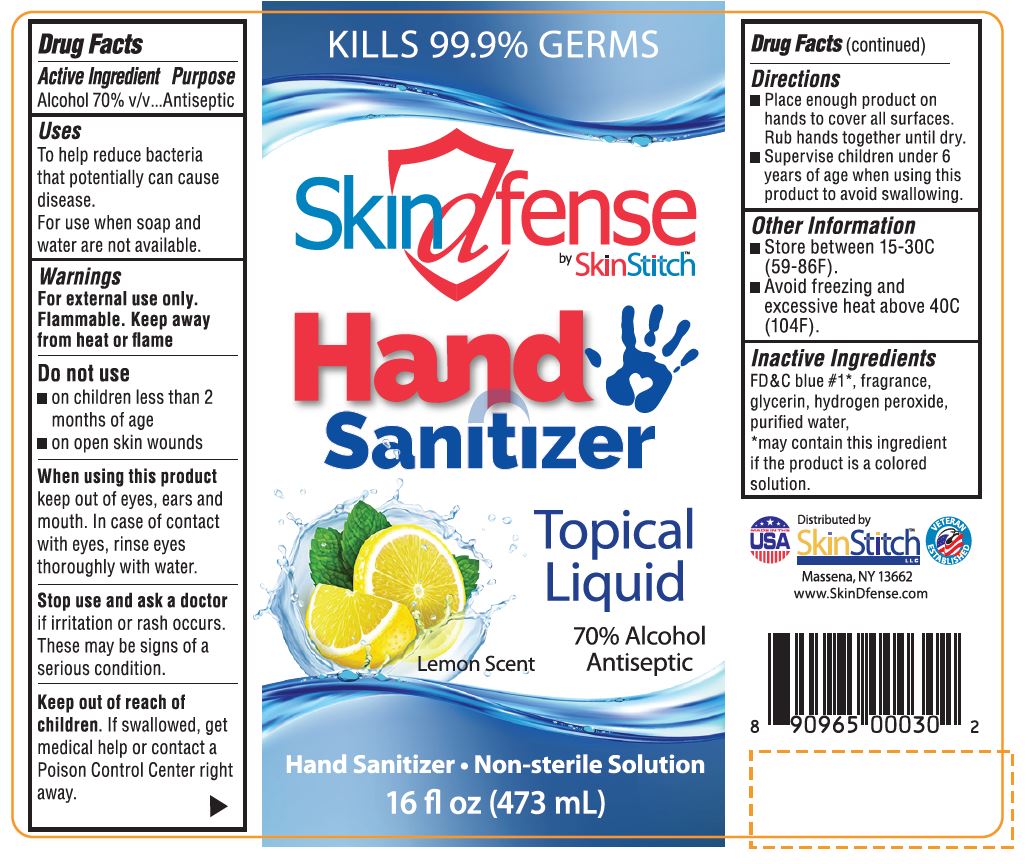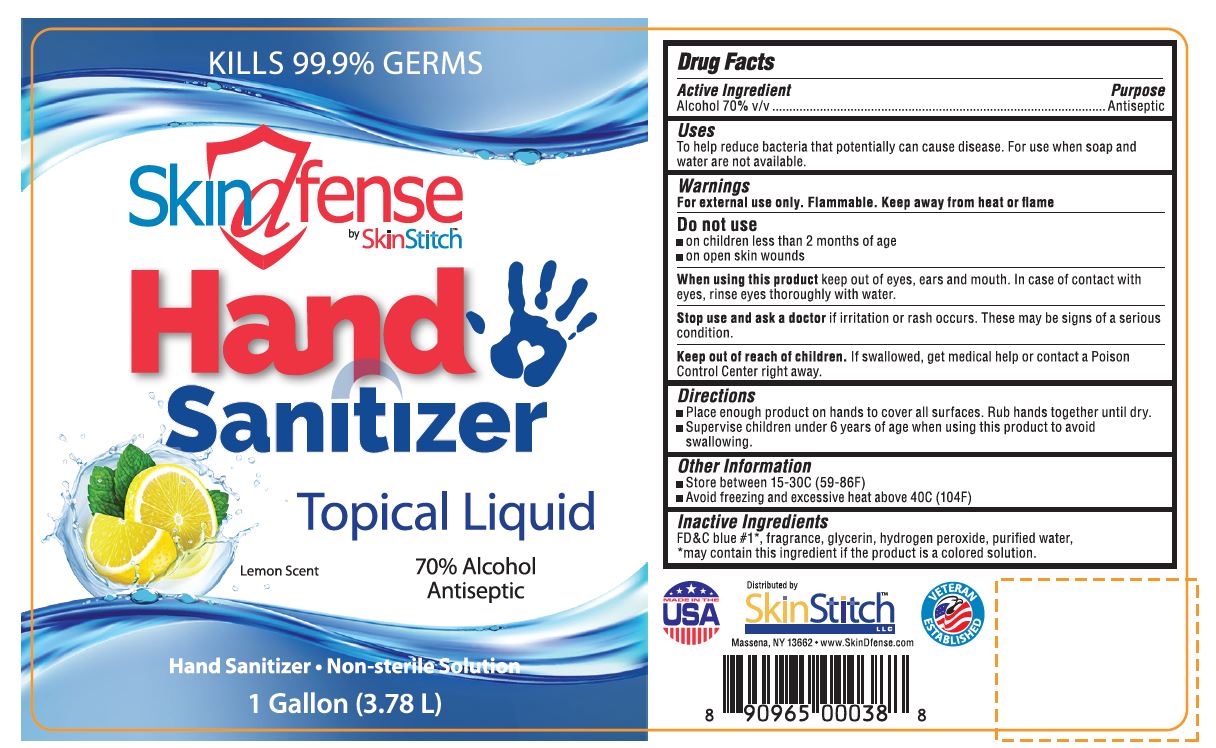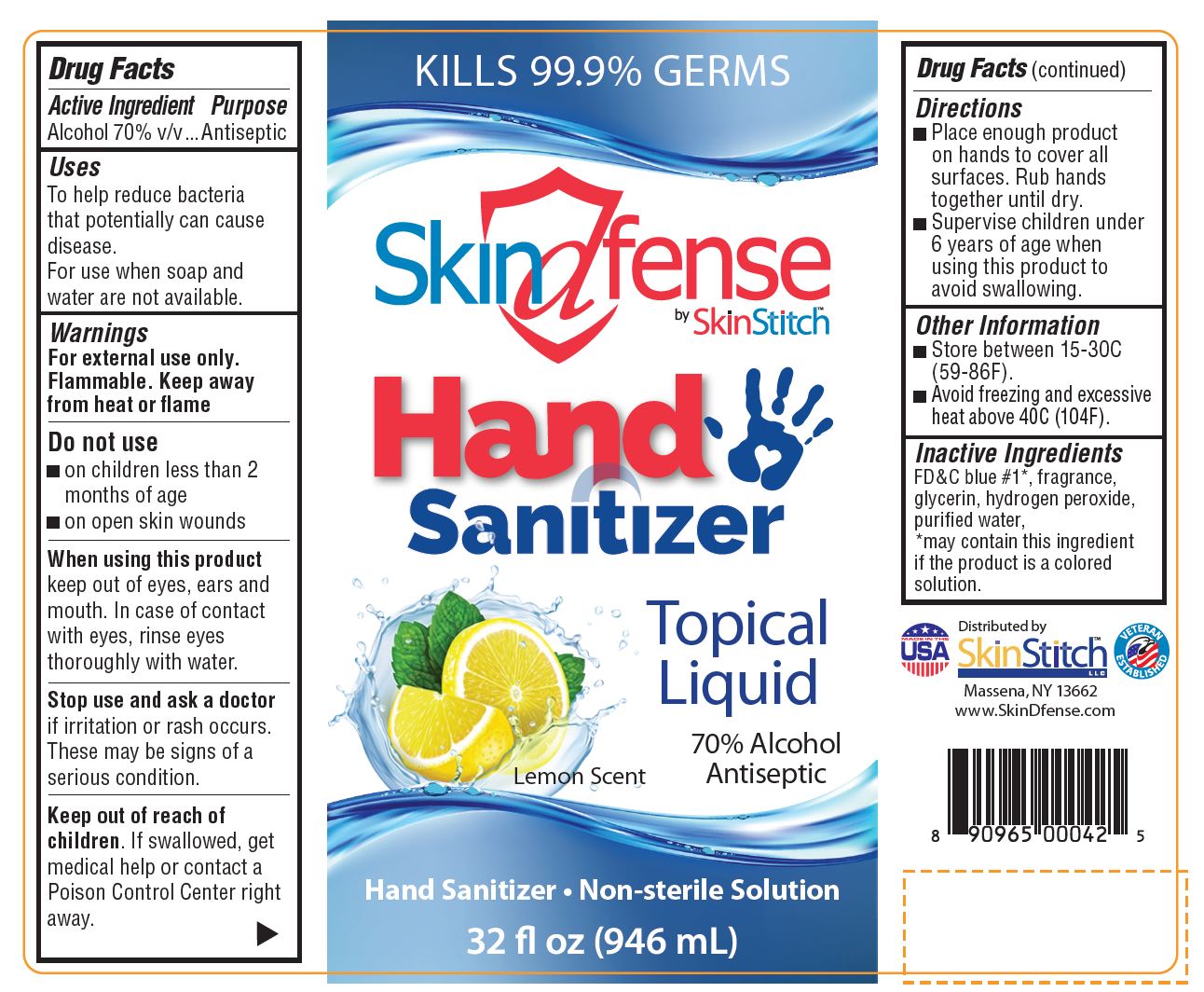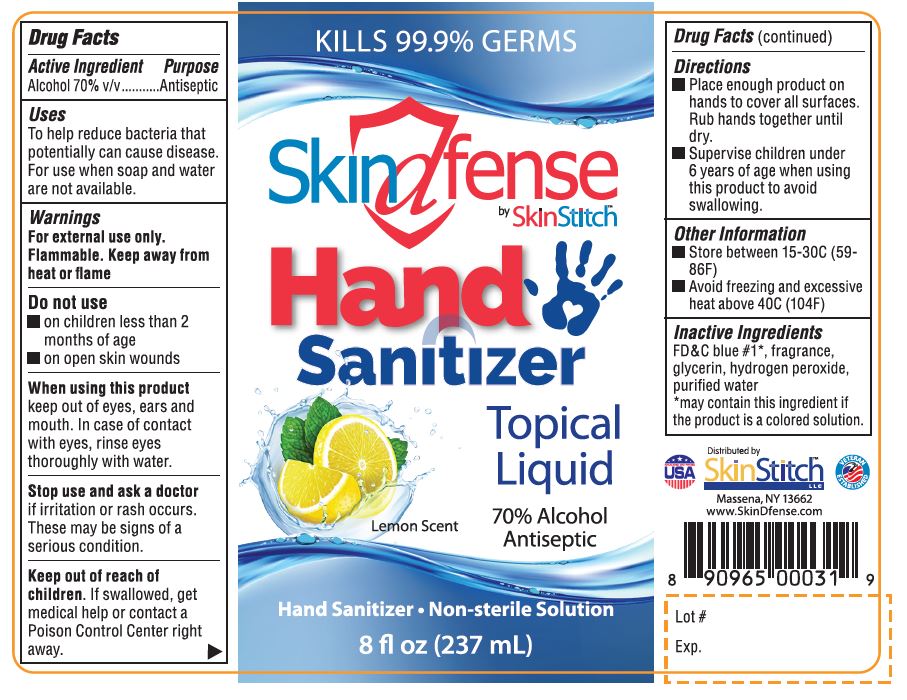 DRUG LABEL: Alcohol Antiseptic
NDC: 73414-057 | Form: SOLUTION
Manufacturer: Seaway Pharma Inc.
Category: otc | Type: HUMAN OTC DRUG LABEL
Date: 20200726

ACTIVE INGREDIENTS: ALCOHOL 70 mL/100 mL
INACTIVE INGREDIENTS: HYDROGEN PEROXIDE; GLYCERIN; FD&C BLUE NO. 1; WATER

Ethylalcohol 70% Hand sanitizer solution

Active Ingredient(s)

Alcohol 70% v/v.............................. Purpose: Antiseptic

Purpose

Antiseptic

Use

Hand Sanitizer to help reduce bacteria that potentially can cause disease. For use when soap and water are not available.

Warnings

For external use only. Flammable. Keep away from heat or flame

Do not use

- on children less than 2 months of age
- on open skin wounds

When using this product keep out of eyes, ears, and mouth. In case of contact with eyes, rinse eyes thoroughly with water.

Stop use and ask a doctor if irritation or rash occurs. These may be signs of a serious condition.

Keep out of reach of children. If swallowed, get medical help or contact a Poison Control Center right away.

Directions

- Place enough product on hands to cover all surfaces. Rub hands together until dry.
- Supervise children under 6 years of age when using this product to avoid swallowing.

Other information

- Store between 15-30C (59-86F)
- Avoid freezing and excessive heat above 40C (104F)

Inactive ingredients

aloe vera gel, amino methyl propanol, carbomer, FD&C blue #1·, FD&C yellow #10·, fragrance, purified water, vitamin E
•may contain one or more of these ingredients if the product is a colored gel.

Package Label - Principal Display Panel

8 fl oz (237 mL) NDC: 73414-057-08

16 fl oz (473 mL) NDC: 73414-057-13

32 fl oz (946 mL) NDC: 73414-057-14

1 Gallon (3.78 L) NDC: 73414-057-91